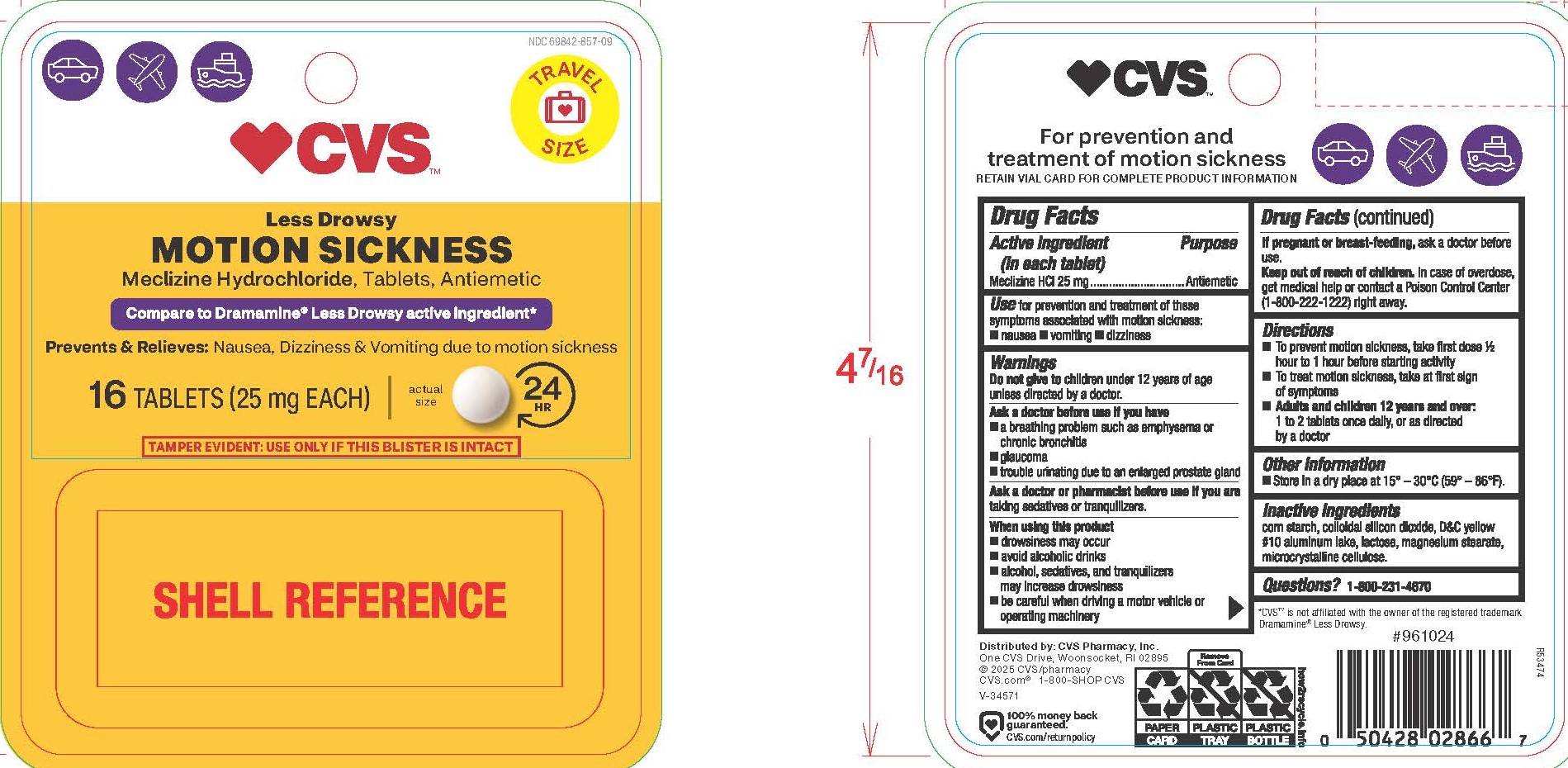 DRUG LABEL: Meclizine Hydrochloride
NDC: 69842-857 | Form: TABLET
Manufacturer: CVS Pharmacy, Inc
Category: otc | Type: HUMAN OTC DRUG LABEL
Date: 20251016

ACTIVE INGREDIENTS: MECLIZINE HYDROCHLORIDE 25 mg/1 1
INACTIVE INGREDIENTS: MAGNESIUM STEARATE; LACTOSE MONOHYDRATE; SILICON DIOXIDE; STARCH, CORN; D&C YELLOW NO. 10 ALUMINUM LAKE; MICROCRYSTALLINE CELLULOSE

5655- CVS

Drug Facts

Active ingredient (in each tablet)
Meclizine HCl 25 mg

Purpose
Antiemetic

Uses

for prevention and treatment of these symptoms associated with motion sickness:
■ nausea ■ vomiting ■ dizziness

WARNINGS

Do not give to

children under 12 years of age unless directed by a doctor.

Ask a doctor before use if you have

■ a breathing problem such as emphysema or chronic bronchitis
■ glaucoma
■ trouble urinating due to an enlarged prostate gland

Ask a doctor or pharmacist before use if you

are taking sedatives or tranquilizers.

When using this product

■ drowsiness may occur
■ avoid alcoholic drinks
■ alcohol, sedatives, and tranquilizers may increase drowsiness
■ be careful when driving a motor vehicle or operating machinery

PREGNANCY OR BREAST FEEDING

If pregnant or breast-feeding, ask a doctor before use.

Keep out of reach of children.

OVERDOSAGE

In case of overdose, get medical help or contact a Poison Control Center (1-800-222-1222) right away.

Directions

■ To prevent motion sickness, take first dose ½ hour to 1 hour before starting activity
■ To treat motion sickness, take at first signs of symptoms
■ Adults and children 12 years and over: 1 to 2 tablets once daily, or as directed by a doctor

Other information

Store in a dry place at 15° – 30°C (59° – 86°F).

INACTIVE INGREDIENT

corn starch, colloidal silicon dioxide, D&C yellow #10 aluminum lake, lactose, magnesium stearate, microcrystalline cellulose

Questions? 1-800-231-4670

For prevention and treatment of motion sickness

RETAIN VIAL CARD FOR COMPLETE PRODUCT INFORMATION

Distributed by: CVS Pharmacy, Inc.
One CVS Drive, Woonsocket, RI 02895
© 2025 CVS/pharmacy
CVS.com® 1-800-SHOP CVS V-34571

*CVS™ is not affiliated with the owner of the registered trademark Dramamine® Less Drowsy.

PACKAGE LABEL

CVS™

NDC 69842-857-09

Less Drowsy

MOTION SICKNESS

Meclizine Hydrochloride, Tablets, Antiemetic

Compare to Dramamine® Less Drowsy active ingredient*

Prevents & Relieves: Nausea, Dizziness & Vomiting due to motion sickness

16 TABLETS (25 mg EACH)

TAMPER EVIDENT: USE ONLY IF THIS BLISTER IS INTACT